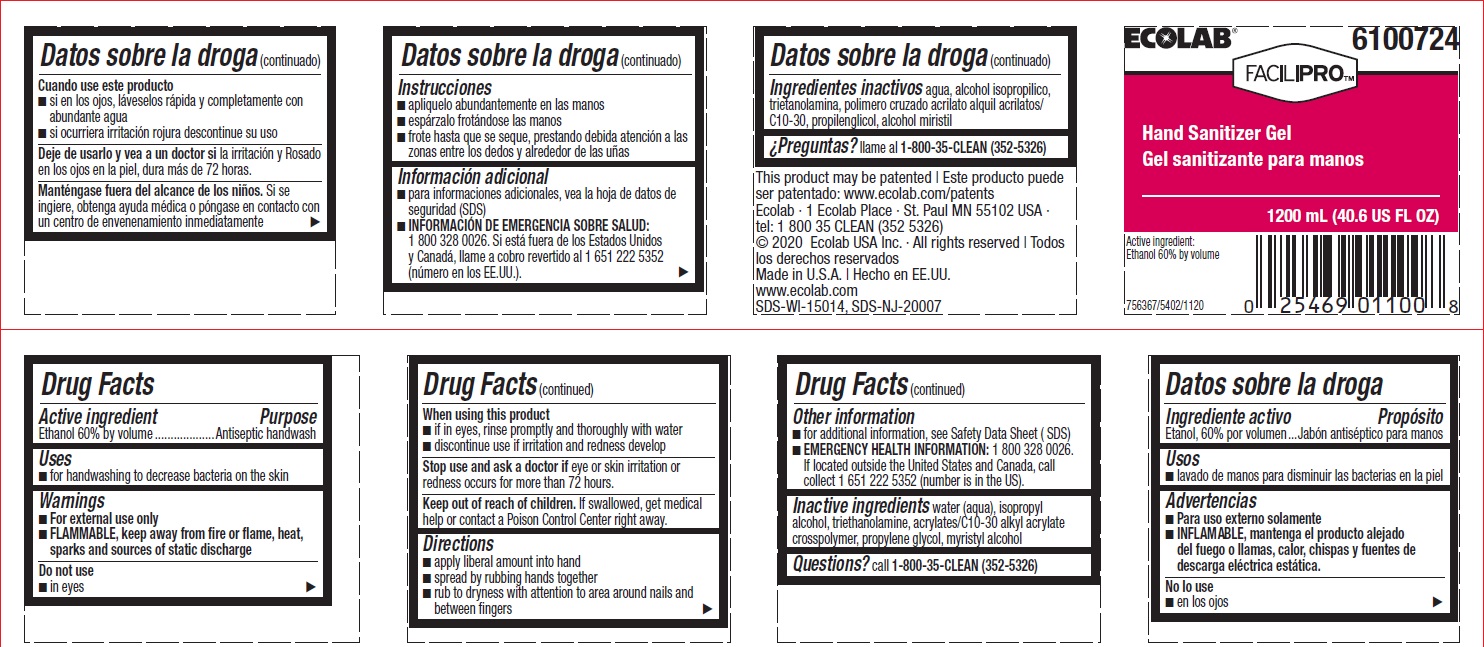 DRUG LABEL: Ecolab
NDC: 47593-508 | Form: LIQUID
Manufacturer: Ecolab Inc.
Category: otc | Type: HUMAN OTC DRUG LABEL
Date: 20240712

ACTIVE INGREDIENTS: ALCOHOL 60 mL/100 mL
INACTIVE INGREDIENTS: WATER; ISOPROPYL ALCOHOL; TROLAMINE; CARBOMER COPOLYMER TYPE B (ALLYL PENTAERYTHRITOL CROSSLINKED); Propylene glycol; MYRISTYL ALCOHOL

Drug Facts

Active ingredient

Ethanol 60% by volume

Purpose

Antiseptic handwash

Uses

- For handwashing to decrease bacteria on the skin

Warnings

- For external use only
- Flammable, keep away from fire or flame, heat, sparks and sources of static discharge

Do not use

- In eyes

When using this product

- If in eyes, rinse promptly and thoroughly with water
- Discontinue use if irritation and redness develop

Stop use and ask a doctor if eye or skin irritation or redness occurs for more than 72 hours

Keep out of reach of children. If swallowed, get medical help or contact a Poison Control Center right away.

Directions

- Apply liberal amount into hand
- Spread by rubbing hands together
- Rub to dryness with attention to area around nails and between fingers

Other information

- For additional information, see Safety Data Sheet (SDS)
- EMERGENCY HEALTH INFORMATION: 1 800 328 0026. If located outside the United States and Canada, call collect 1 651 222 5352 (number is in the US).

INACTIVE INGREDIENT

Inactive ingredients water (aqua), isopropyl alcohol, triethanolamine, acrylates/C10-30 alkyl acrylate crosspolymer, propylene glycol, myristyl alcohol

Questions? call 1-800-35-CLEAN (352-5326)

Principal display panel and representative label

ECOLAB

6100724

FACILIPRO

HAND SANITIZER GEL

1200 ML (40.6 US FL OZ)

Active Ingredient: Ethanol 60% by volume

Ecolab · 1 Ecolab Place · St. Paul MN 55102 USA · tel: 1 800 35 CLEAN (352 5326)

© 2020 Ecolab USA Inc. · All rights reserved | Todos los derechos reservados

Made in U.S.A. | Hecho en EE.UU.

www.ecolab.com

SDS-WI-15014, SDS-NJ-20007